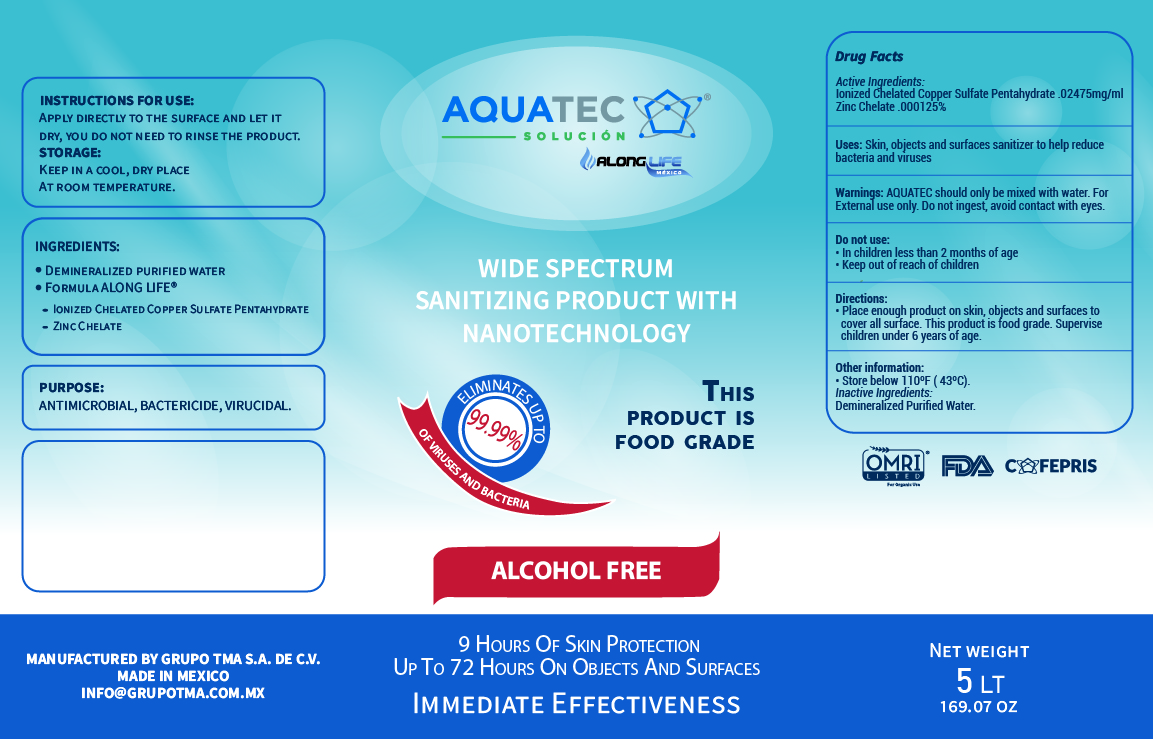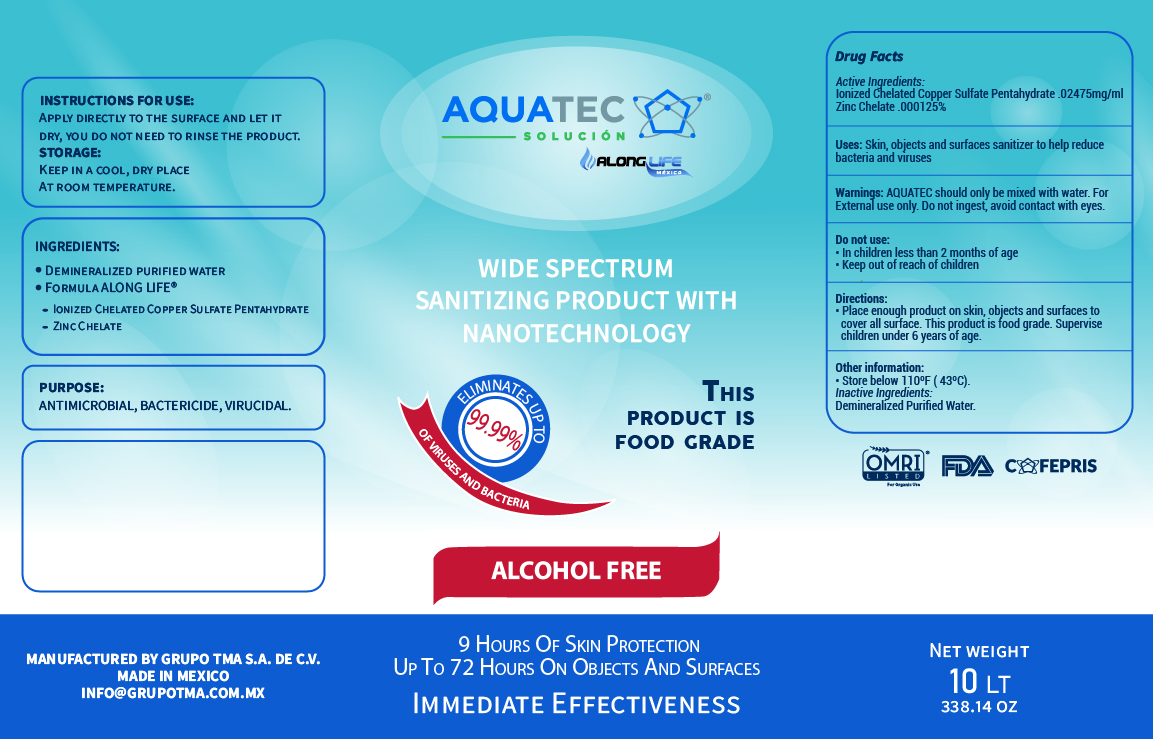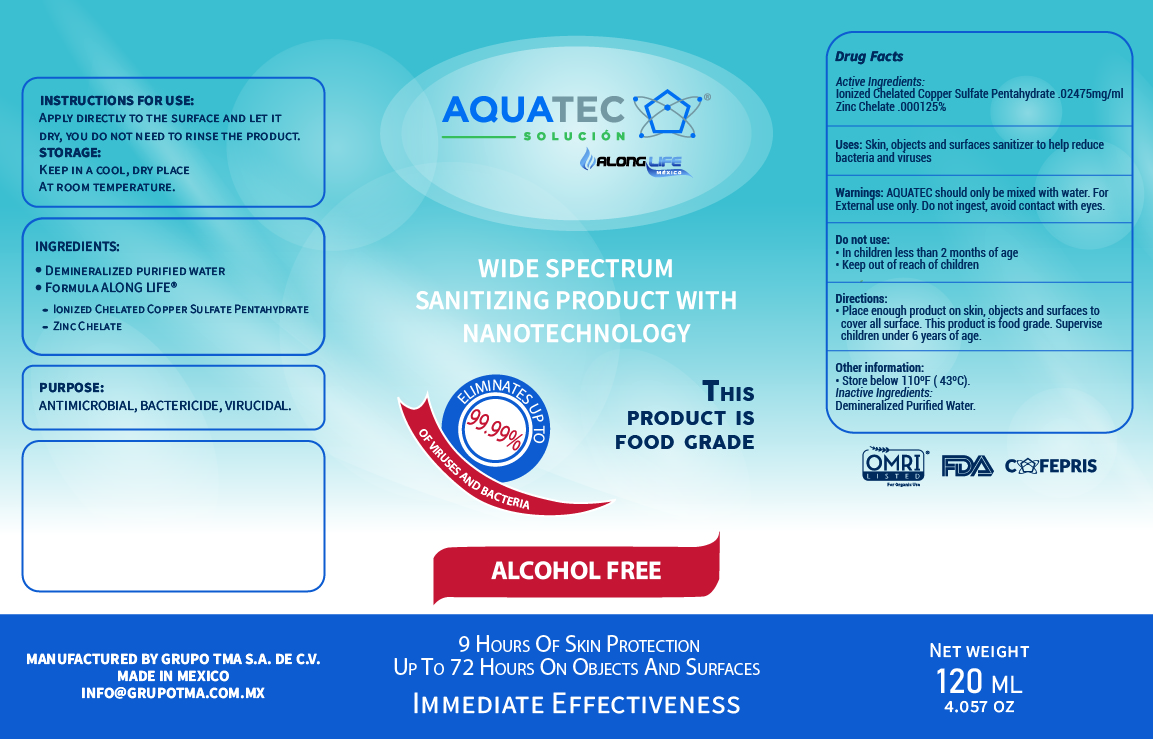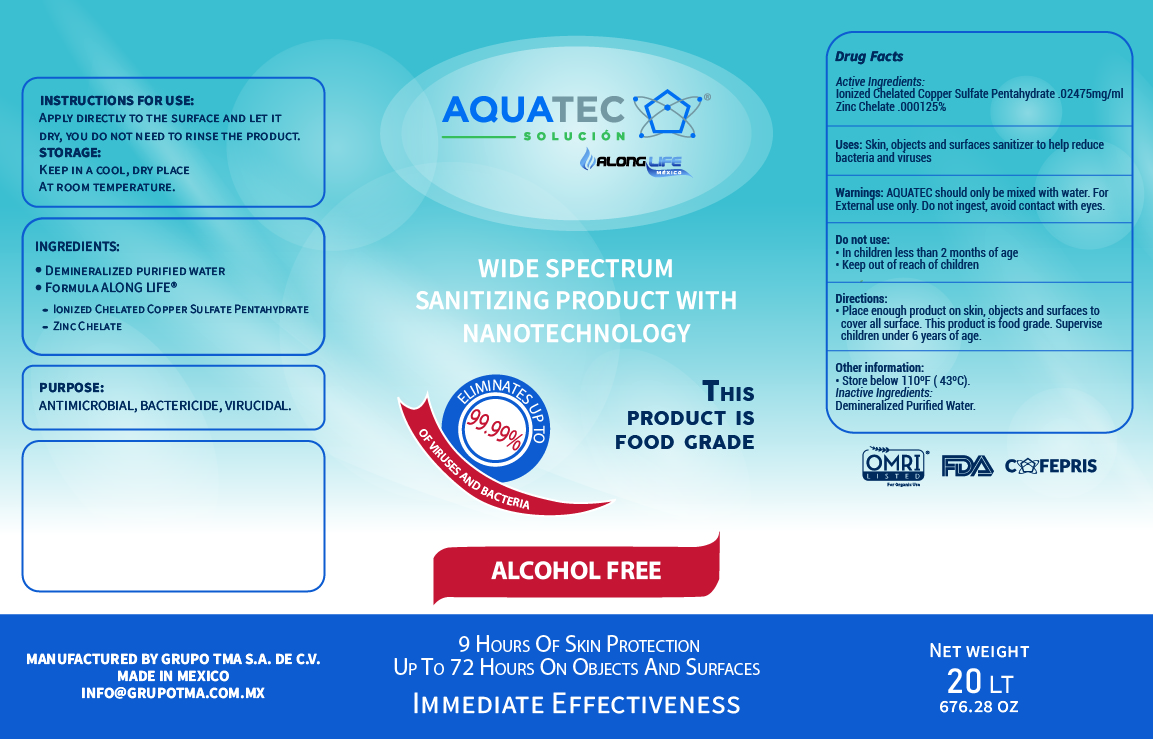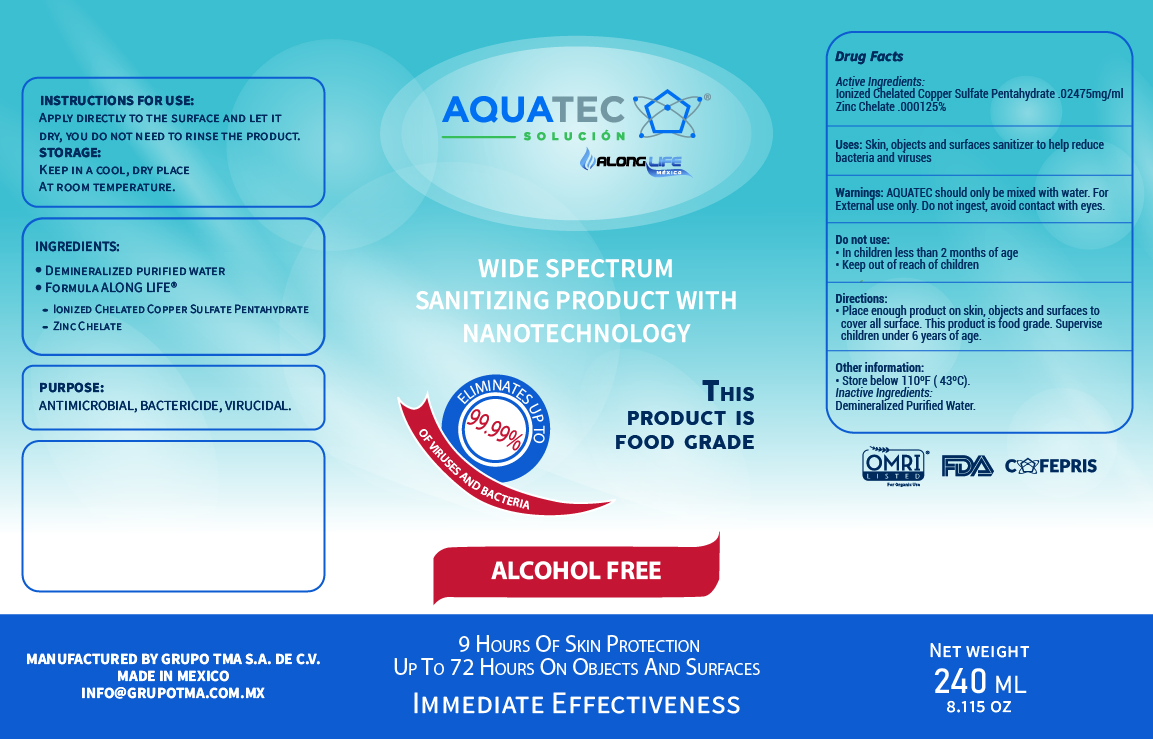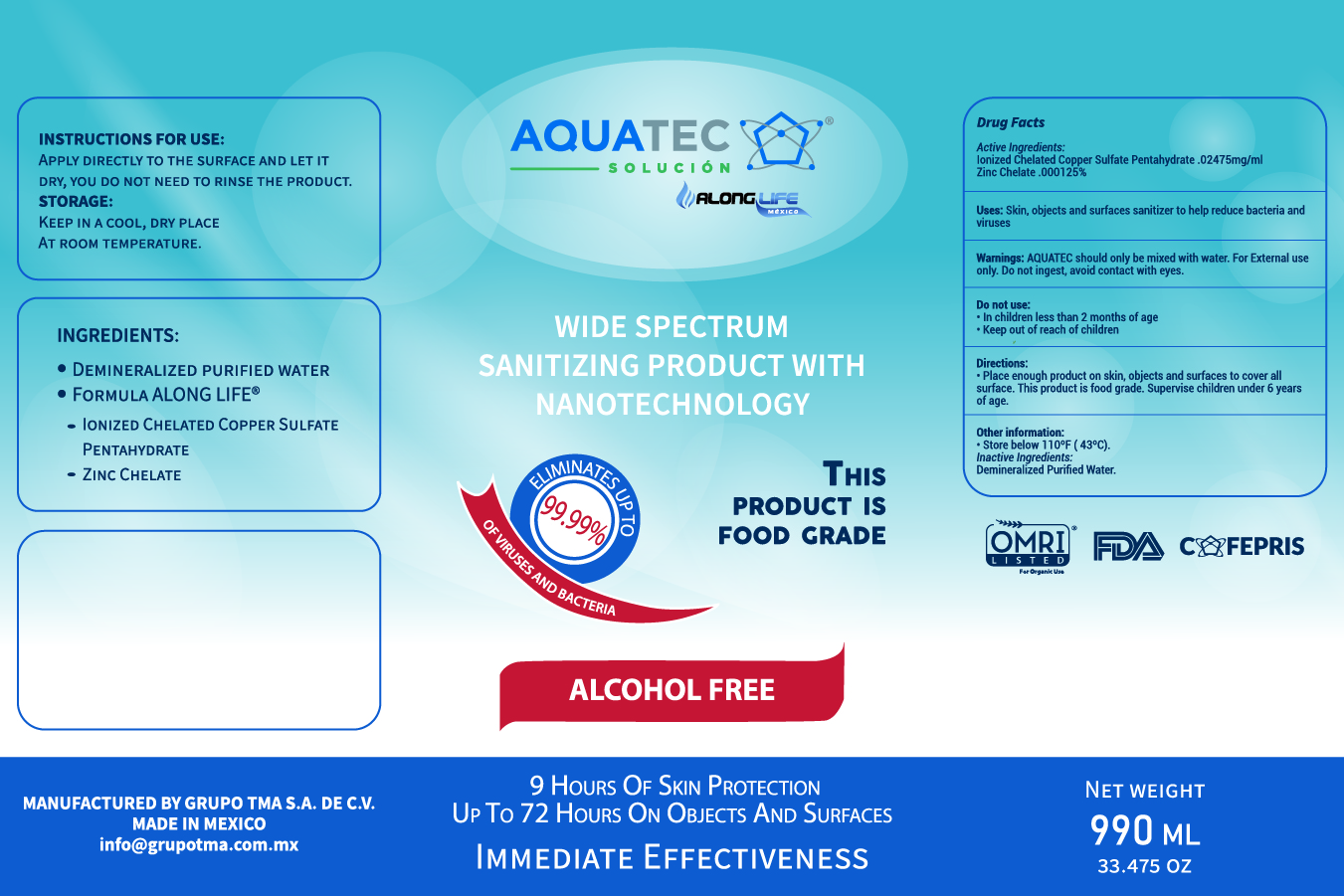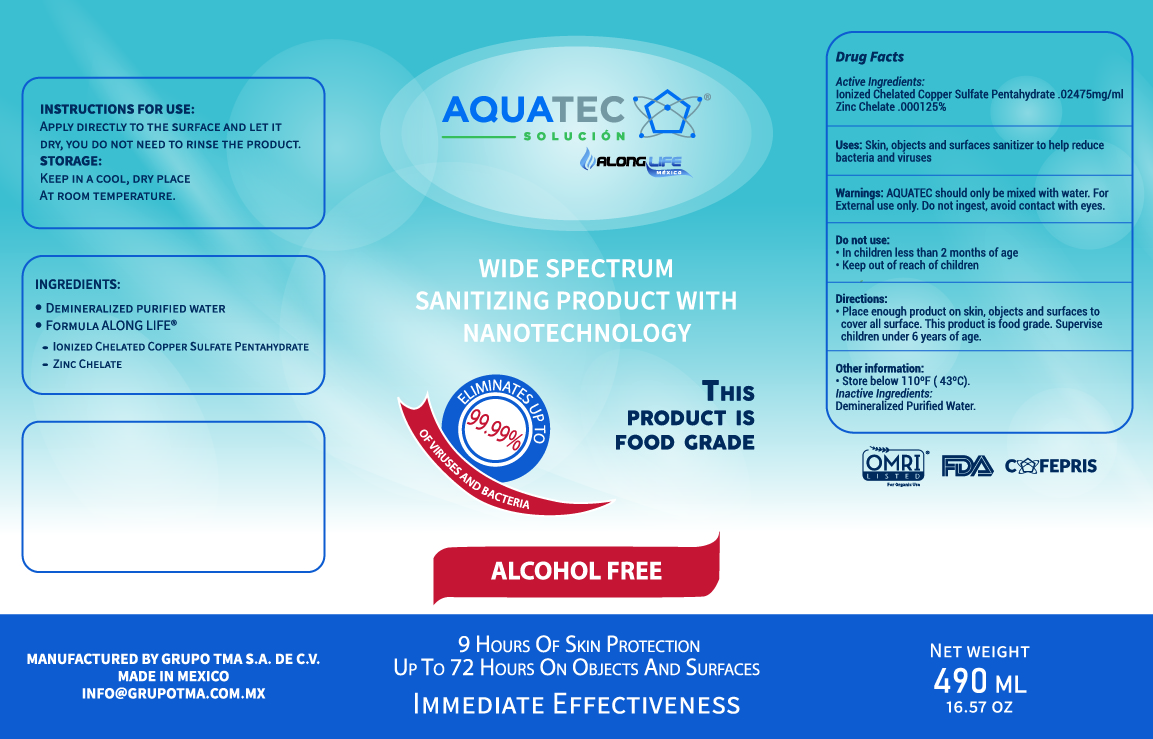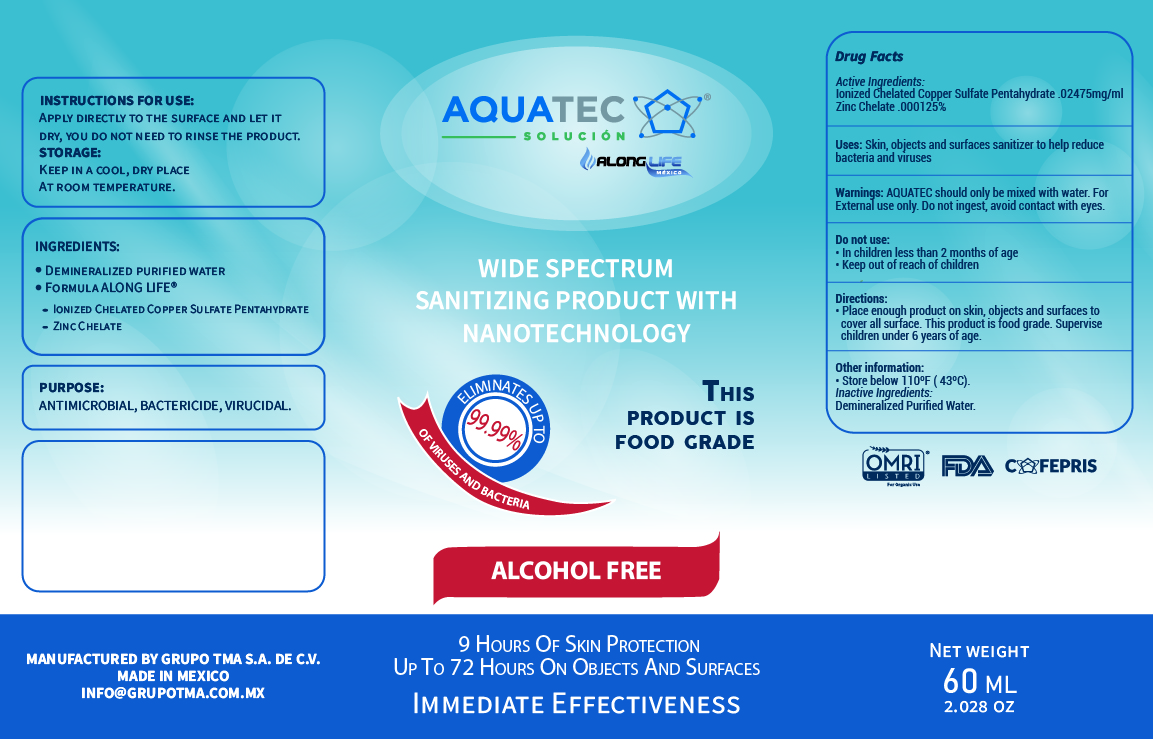 DRUG LABEL: AQUATEC  ALONGLIFE
NDC: 80224-1000 | Form: SOLUTION
Manufacturer: GRUPO TMA TECNOLOGIAS PARA EL MEJORAMIENTO DEL AGUA S.A. DE C.V.
Category: otc | Type: HUMAN OTC DRUG LABEL
Date: 20210215

ACTIVE INGREDIENTS: CUPRIC SULFATE 0.02475 mg/1 mL
INACTIVE INGREDIENTS: WATER 0.975125 mL/1 mL; ZINC 0.000125 mL/1 mL

AQUATEC SOLUTION ALONGLIFE SANITIZER

ACTIVE INGREDIENT SECTION

ACTIVE INGREDIENT

Active ingredient Chelated Copper Sulfate Pentahydrate .02475 %

PURPOSE

Purpose Antmicrobial, Bactericide, Virucidal

INDICATION AND USAGE

Use[s]

Skin, objects and surface sanitizer to help reduce bacteria and viruses

DOSAGE AND ADMINISTRATION

Directions

Place enough product on skin, objects and surfaces to cover all surface. This product is food grade. Supervise children under 6 years of age.

WARNINGS AND PRECAUTIONS

AQUATEC should only be mixed with water. For external use only. Don not ingest, avoid contact with eyes.

KEEP OUT OF REACH OF CHILDREN

WARNINGS

For external use only.

AQUATEC should only be mixed with water. For external use only. Don not ingest, avoid contact with eyes.

INACTIVE INGREDIENTS

Inactive ingredients: Purified demineralized water, Zinc Chelate

DO NOT USE

In children less than 2 months of age.